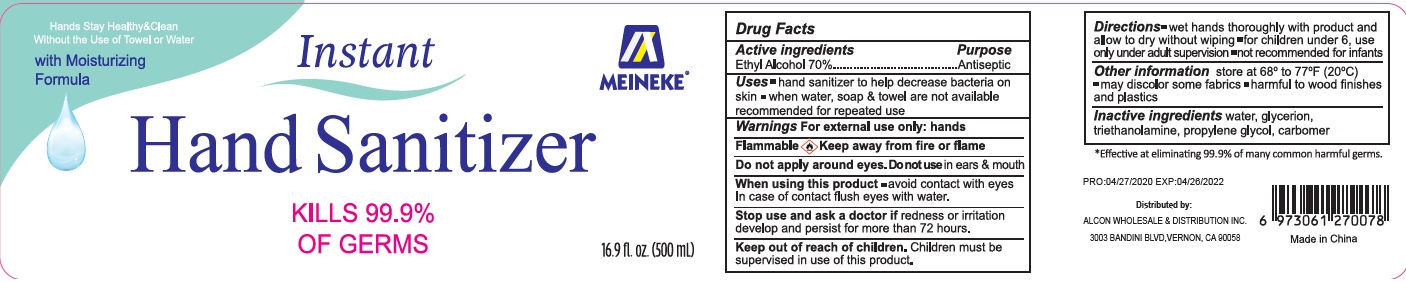 DRUG LABEL: Meineke Instant Hand Sanitizer With Moisturizing Formula
NDC: 52174-018 | Form: GEL
Manufacturer: Ningbo BST Clean And Care Products Co., Ltd
Category: otc | Type: HUMAN OTC DRUG LABEL
Date: 20200514

ACTIVE INGREDIENTS: alcohol 70 mL/100 mL
INACTIVE INGREDIENTS: WATER; PROPYLENE GLYCOL; TROLAMINE; CARBOMER 934; GLYCERIN

Drug facts

Active ingredient Purpose

Ethyl Alcohol 70% ... Antiseptic

USES:

- Hand sanitizer to help decrease bacteria on the skin
- When water, soap and towel are not available
- Recommended for repeated use

KEEP OUT OF REACH OF CHILDREN

Children must be supervised in use of this product.

INDICATIONS AND USAGE

- Wet hands thoroughly with product and allow to dry without wiping.
- For children under 6, use only under adult supervision
- Not recommended for infants

WARNINGS

For external use only.
Flammable. Keep away from fire or flame.

Do not apply around eyes. Do not use in ears and mouth.

When using this products

- avoid contact with eyes. In case of contact, flush eyes with water.

Stop using and ask a doctor, if redness or irritation develop and persist for more than 72 hours.

Other information:

- Store at 68-77℉（20℃）
- May discolor certain fabrics
- harmful to wood finishes and plastics

DOSAGE AND ADMINISTRATION

for children under 6, use only under adult supervision.

INACTIVE INGREDIENT

Water, glycerion, Triethanolamine, propylene glycol, carbomer